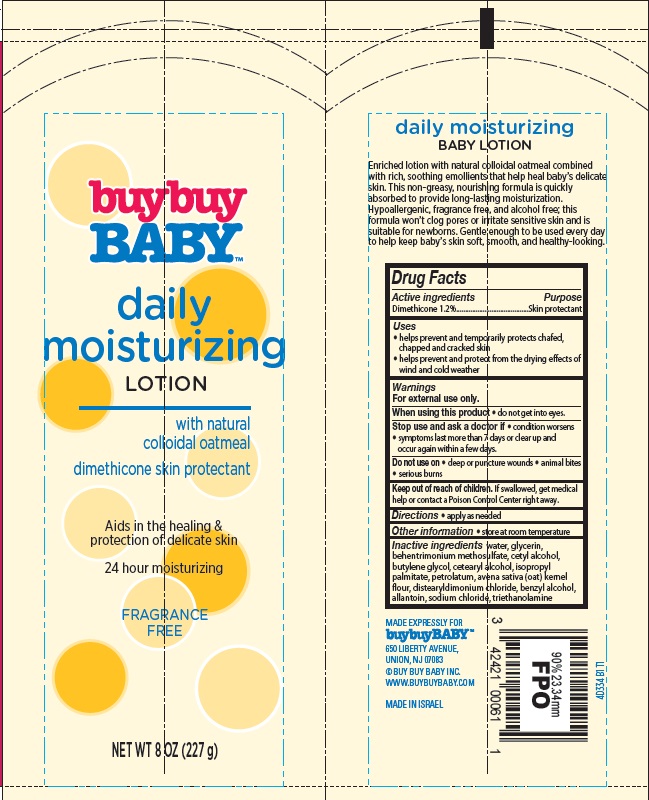 DRUG LABEL: Baby Daily Moisturizing Fragrance Free
NDC: 63940-433 | Form: LOTION
Manufacturer: Harmon Stores Inc.
Category: otc | Type: HUMAN OTC DRUG LABEL
Date: 20140905

ACTIVE INGREDIENTS: DIMETHICONE 1.2 g/100 mL
INACTIVE INGREDIENTS: WATER; GLYCERIN; BEHENTRIMONIUM METHOSULFATE; CETYL ALCOHOL; BUTYLENE GLYCOL; CETOSTEARYL ALCOHOL; ISOPROPYL PALMITATE; PETROLATUM; OATMEAL; DISTEARYLDIMONIUM CHLORIDE; BENZYL ALCOHOL; ALLANTOIN; SODIUM CHLORIDE; TROLAMINE

Baby Daily Moisturizing Fragrance Free

Active ingredient

Dimethicone 1.2%

Purpose

Skin protectant

Uses

- helps prevent and temporarily protects chafed, chapped and cracked skin
- helps prevent and protect from the drying effects of wind and cold weather

Warnings

For external use only.

When using this product

- do not get into eyes.

Stop use and ask a doctor if

- condition worsens
- symptoms last more than 7 days or clear up and occur again within a few days.

Do not use on

- deep or puncture wounds
- animal bites
- serious burns

Keep Out of Reach of Children.

If swallowed, get medical help or contact a Poison Control Center right away.

Directions

- apply as needed

Other Information

- store at room temperature

Inactive ingredients

water, glycerin, behentrimonium methosulfate, cetyl alcohol, butylene glycol, cetearyl alcohol, isopropyl palmitate, petrolatum, avena sativa (oat) kernel flour, distearyldimonium chloride, benzyl alcohol, allantoin, sodium chloride, triethanolamine

Package/Label Principal Display Panel

buybuy
BABY™

daily
moisturizing
LOTION

with natural
colloidal oatmeal

dimethicone skin protectant

Aids in the healing & protection of delicate skin

24 hour moisturizing

FRAGRANCE
FREE

NET WT 8 OZ (227 g)

daily moisturizing
BABY LOTION

Enriched lotion with natural colloidal oatmeal combined with rich, soothing emollients that help heal baby’s delicate skin. This non-greasy, nourishing formula is quickly absorbed to provide long-lasting moisturization. Hypoallergenic, fragrance free, and alcohol free; this formula won’t clog pores or irritate sensitive skin and is suitable for newborns. Gentle enough to be used every day to help keep baby’s skin soft, smooth, and healthy-looking.

MADE EXPRESSLY FOR
buybuyBABY™
650 LIBERTY AVENUE,
UNION, NJ 07083
© BUY BUY BABY INC.
WWW.BUYBUYBABY.COM

MADE IN ISRAEL

4D334 B1 T1

Carton Label